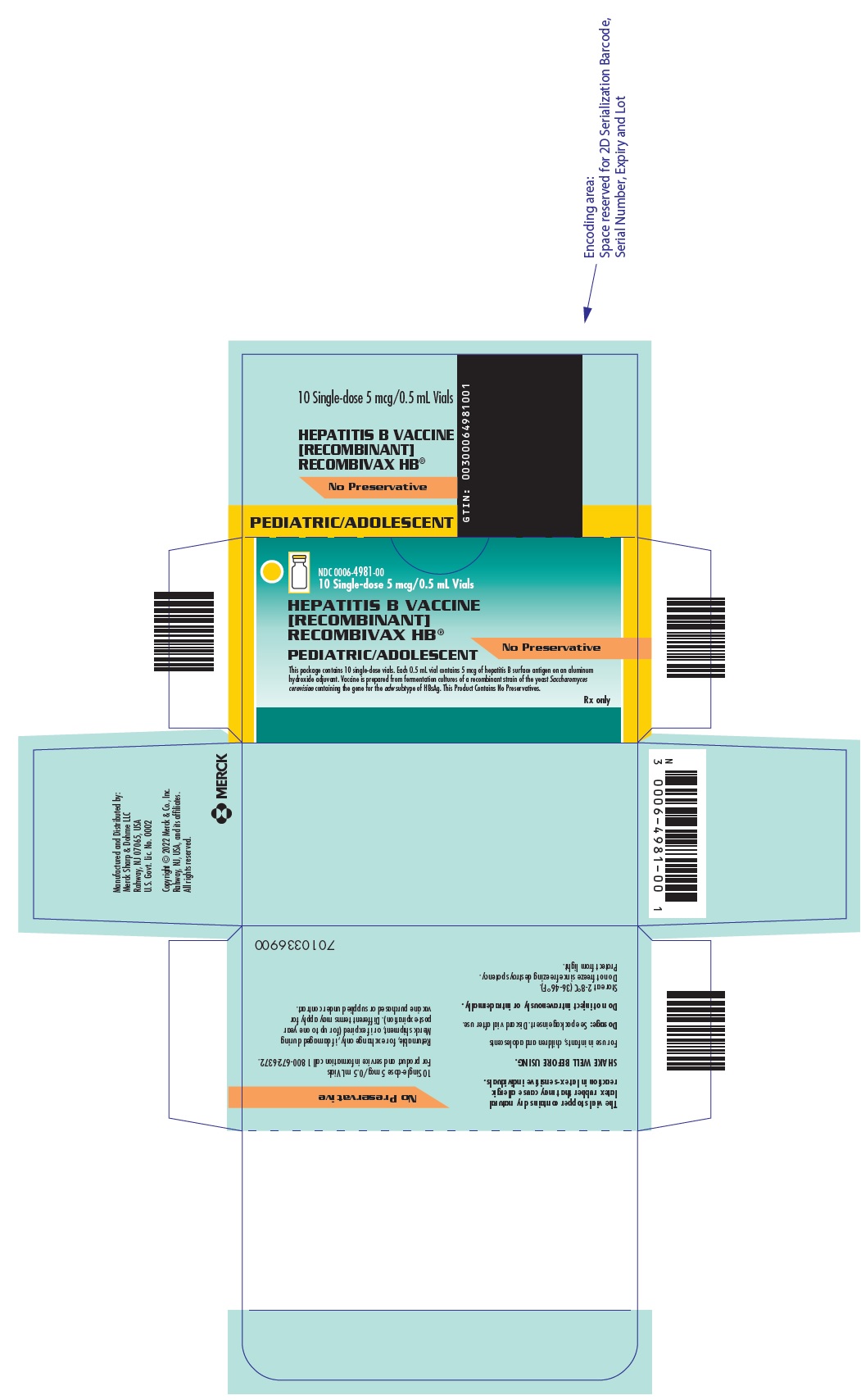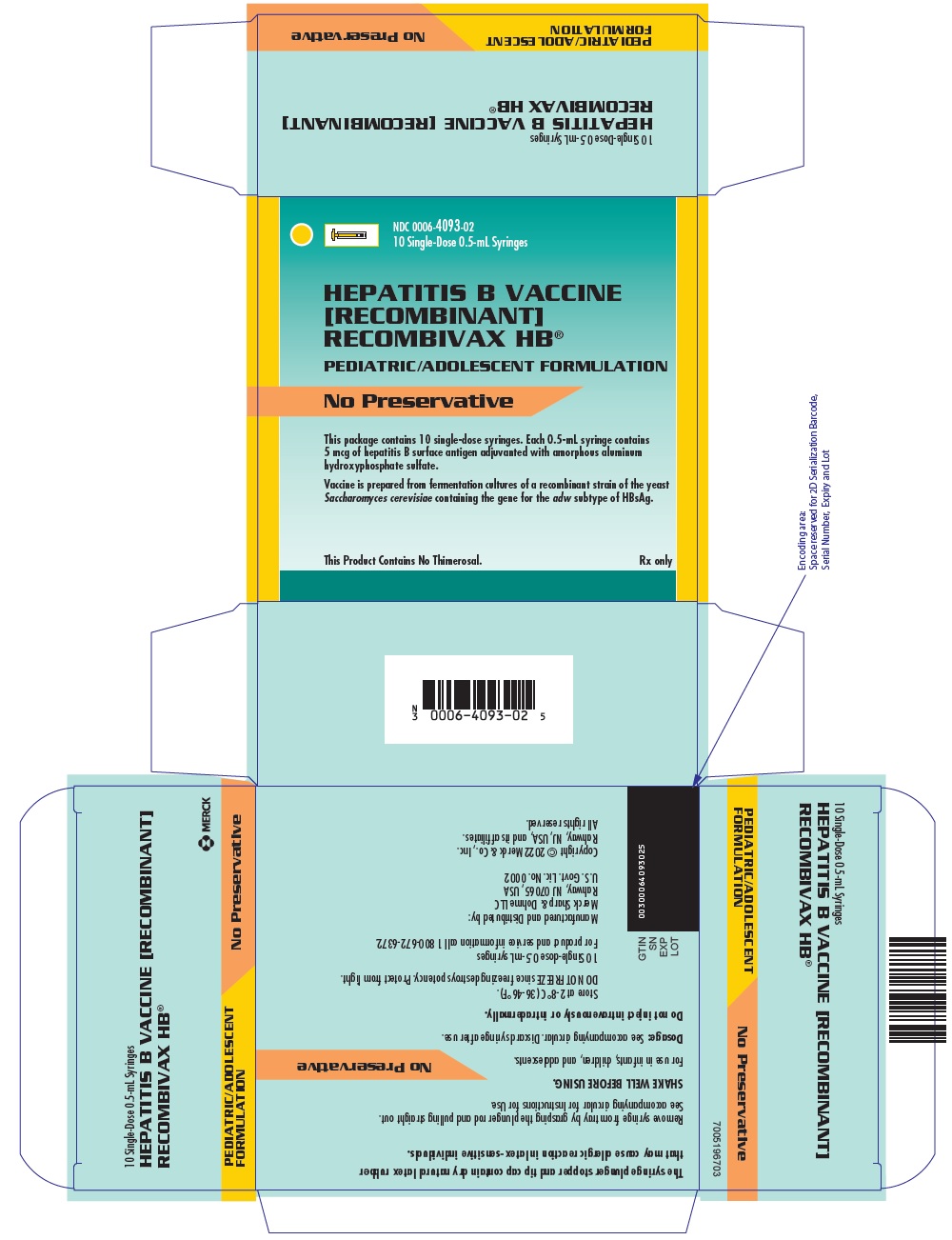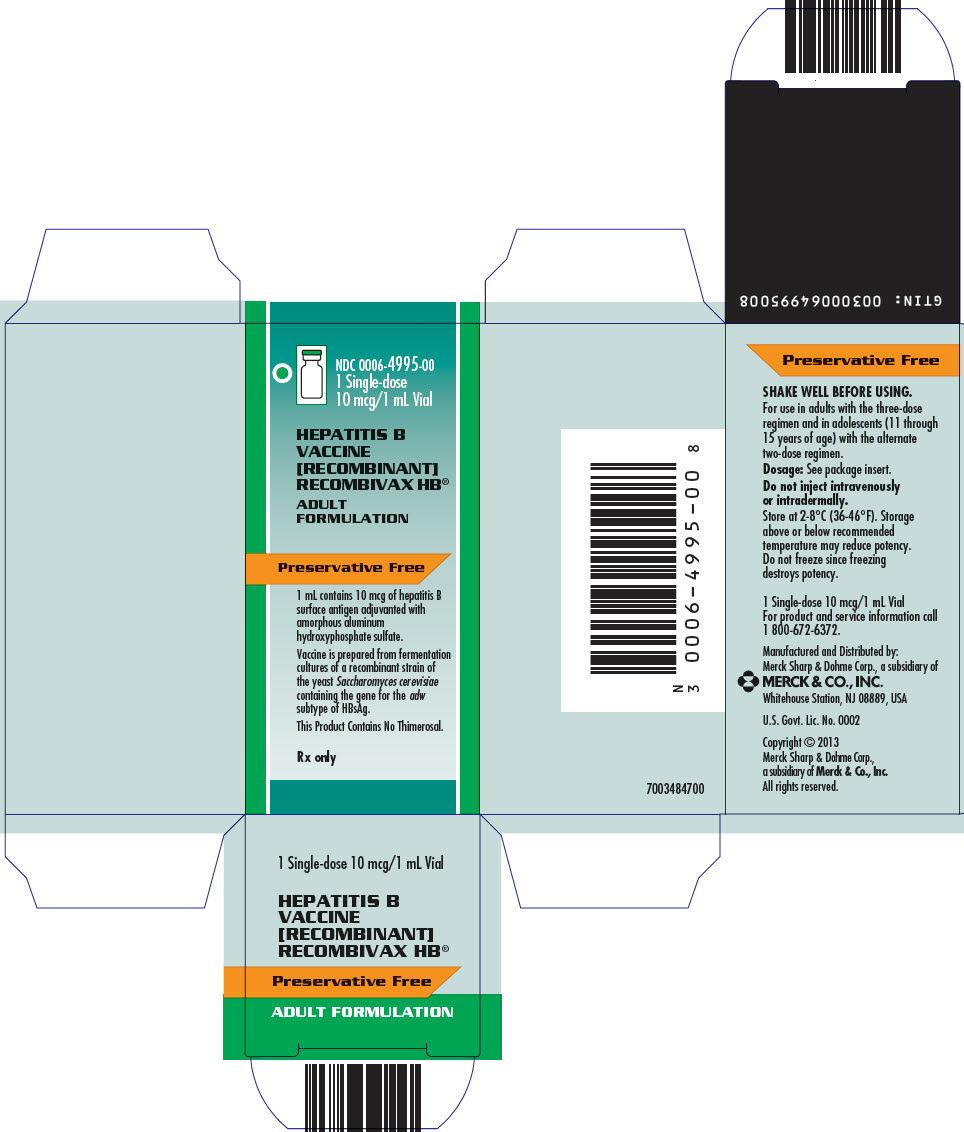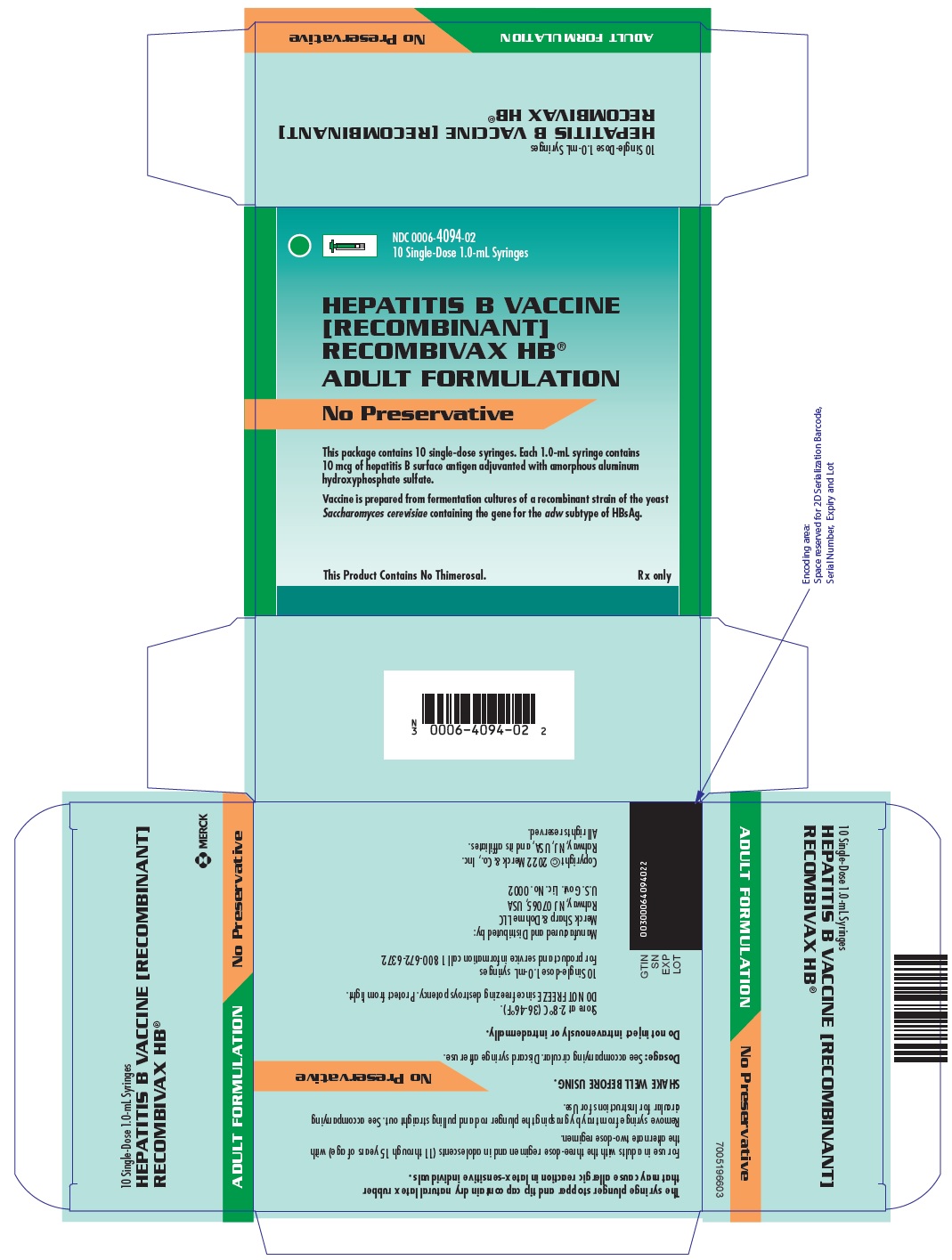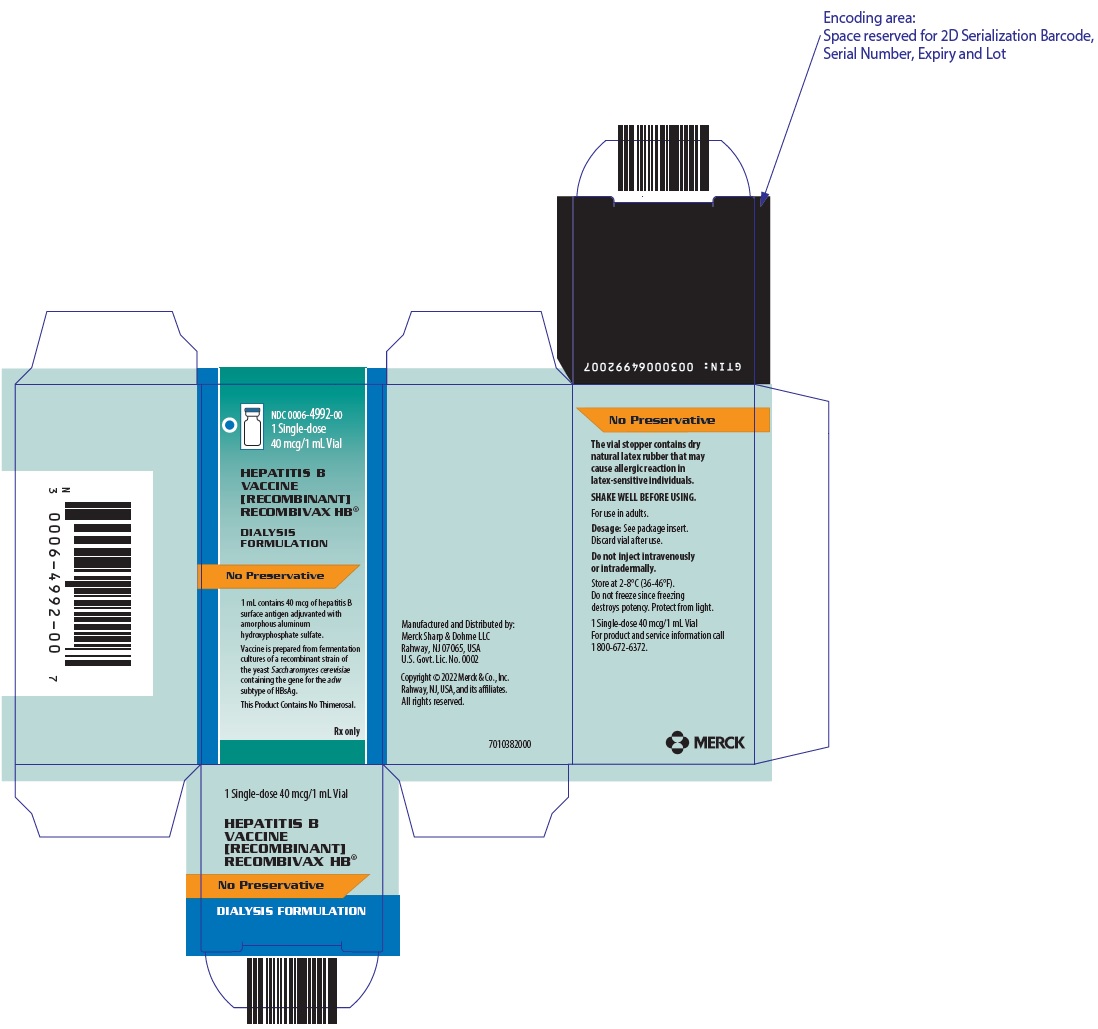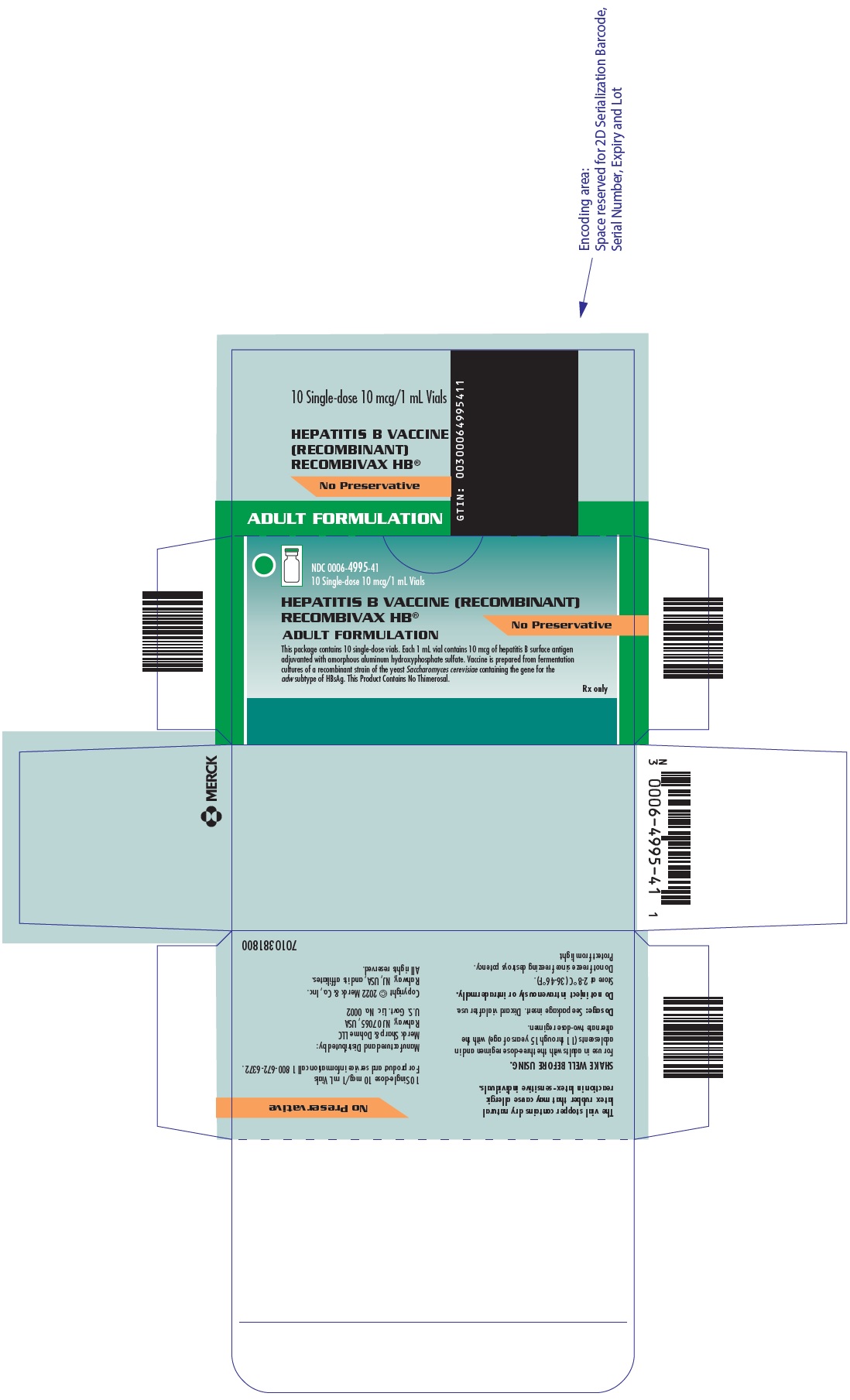 DRUG LABEL: RECOMBIVAX HB
NDC: 0006-4981 | Form: INJECTION, SUSPENSION
Manufacturer: Merck Sharp & Dohme LLC
Category: other | Type: VACCINE LABEL
Date: 20241031

ACTIVE INGREDIENTS: HEPATITIS B VIRUS SUBTYPE ADW HBSAG SURFACE PROTEIN ANTIGEN 5 ug/0.5 mL

HIGHLIGHTS OF PRESCRIBING INFORMATION

These highlights do not include all the information needed to use RECOMBIVAX HB safely and effectively. See full prescribing information for RECOMBIVAX HB.
RECOMBIVAX HB® Hepatitis B Vaccine (Recombinant)
Suspension for intramuscular injection
Initial U.S. Approval: 1986

1 INDICATIONS AND USAGE

RECOMBIVAX HB is a vaccine indicated for prevention of infection caused by all known subtypes of hepatitis B virus. RECOMBIVAX HB is approved for use in individuals of all ages. RECOMBIVAX HB Dialysis Formulation is approved for use in predialysis and dialysis patients 18 years of age and older. (1)

2 DOSAGE AND ADMINISTRATION

RECOMBIVAX HB

- Persons from birth through 19 years of age: A series of 3 doses (0.5 mL each) given on a 0-, 1-, and 6-month schedule. (2.1)
- Adolescents 11 through 15 years of age: A series of either 3 doses (0.5 mL each) given on a 0-, 1-, and 6-month schedule or a series of 2 doses (1.0 mL) on a 0- and 4- to 6-month schedule). (2.1)
- Persons 20 years of age and older: A series of 3 doses (1.0 mL each) given on a 0-, 1-, and 6-month schedule. (2.1)

RECOMBIVAX HB Dialysis Formulation

- Adults on predialysis or dialysis: A series of 3 doses (1.0 mL each) given on a 0-, 1-, and 6-month schedule. (2.1)

3 DOSAGE FORMS AND STRENGTHS

RECOMBIVAX HB is a sterile suspension available in the following presentations:

- 0.5 mL (5 mcg) Pediatric/Adolescent Formulation single-dose vials and prefilled syringes (3, 11, 16.1)
- 1 mL (10 mcg) Adult Formulation single-dose vials and prefilled syringes (3, 11, 16.1)

RECOMBIVAX HB Dialysis Formulation is a sterile suspension available in the following presentation:

- 1 mL (40 mcg) single-dose vials (3, 11, 16.1)

4 CONTRAINDICATIONS

Severe allergic or hypersensitivity reactions (e.g., anaphylaxis) after a previous dose of any hepatitis B-containing vaccine, or to any component of RECOMBIVAX HB, including yeast. (4, 11)

5 WARNINGS AND PRECAUTIONS

The vial stopper, the syringe plunger stopper, and tip cap contain dry natural latex rubber which may cause allergic reactions in latex-sensitive individuals. (5.1)

Apnea following intramuscular vaccination has been observed in some infants born prematurely. Decisions about when to administer an intramuscular vaccine, including RECOMBIVAX HB, to infants born prematurely should be based on consideration of the individual infant's medical status and the potential benefits and possible risks of vaccination. (5.2)

6 ADVERSE REACTIONS

In healthy infants and children (up to 10 years of age), the most frequently reported systemic adverse reactions (>1% injections), in decreasing order of frequency, were irritability, fever, diarrhea, fatigue/weakness, diminished appetite, and rhinitis. (6.1)

In healthy adults, injection site reactions and systemic adverse reactions were reported following 17% and 15% of the injections, respectively. (6.1)

To report SUSPECTED ADVERSE REACTIONS, contact Merck Sharp & Dohme LLC at 1-877-888-4231 or VAERS at 1-800-822-7967 or www.vaers.hhs.gov .

7 DRUG INTERACTIONS

Do not mix RECOMBIVAX HB with any other vaccine in the same syringe or vial. (7.1)

FULL PRESCRIBING INFORMATION

1 INDICATIONS AND USAGE

RECOMBIVAX HB® [Hepatitis B Vaccine, Recombinant] is indicated for prevention of infection caused by all known subtypes of hepatitis B virus. RECOMBIVAX HB is approved for use in individuals of all ages. RECOMBIVAX HB Dialysis Formulation is approved for use in adult predialysis and dialysis patients 18 years of age and older.

2 DOSAGE AND ADMINISTRATION

For intramuscular administration. See Section 2.2 for subcutaneous administration in persons with hemophilia.

RECOMBIVAX HB should be administered as soon as possible after being removed from refrigeration [see How Supplied/Storage and Handling (16)].

2.1 Dosage and Schedule

RECOMBIVAX HB:

Persons from birth through 19 years of age: A series of 3 doses (0.5 mL each) given on a 0-, 1-, and 6-month schedule.

Adolescents 11 through 15 years of age: A series of 3 doses (0.5 mL each) given on a 0-, 1-, and 6-month schedule or a series of 2 doses (1.0 mL each) on a 0- and 4- to 6-month schedule.

Persons 20 years of age and older: A series of 3 doses (1.0 mL each) given on a 0-, 1-, and 6-month schedule.

RECOMBIVAX HB Dialysis Formulation:

Adults on predialysis and dialysis: A series of 3 doses (1.0 mL each) given on a 0-, 1-, and 6-month schedule.

Table 1 summarizes the dose and formulation of RECOMBIVAX HB for specific populations, regardless of the risk of infection with hepatitis B virus.

Table 1: RECOMBIVAX HB Recommended Dose and Administration Schedules
Group | Dose/Regimen
Infants [For specific recommendations for infants see ACIP recommendations.{1}] , Children and Adolescents 0-19 years of age (Pediatric/Adolescent Formulation) | 5 mcg (0.5 mL) 3 doses at 0, 1, and 6 months
Adolescents [Adolescents (11 through 15 years of age) may receive either regimen: 3 × 5 mcg (Pediatric Formulation) or 2 × 10 mcg (Adult Formulation).] 11 through 15 years of age (Adult Formulation) | 10 mcg [If the suggested dose (10 mcg) is not available, the appropriate dosage can be achieved with two 5 mcg doses. However, the Dialysis Formulation may be used only for adult predialysis/dialysis patients.] (1.0 mL) 2 doses at 0 and 4-6 months
Adults ≥20 years of age (Adult Formulation) | 10 mcg (1.0 mL) 3 doses at 0, 1, and 6 months
Predialysis and Dialysis Patients [See also recommendations for revaccination of predialysis and dialysis patients in [Dosage and Administration (2.4)].] (Dialysis Formulation) | 40 mcg (1.0 mL) 3 doses at 0, 1, and 6 months

2.2 Preparation and Administration

Shake the single-dose vial or single-dose prefilled syringe well to obtain a slightly opaque, white suspension before withdrawal and use. Parenteral drug products should be inspected visually for particulate matter and discoloration prior to administration, whenever solution and container permit. Discard if the suspension does not appear homogeneous or if extraneous particulate matter remains or if discoloration is observed.

For single-dose vials, withdraw and administer entire dose of RECOMBIVAX HB intramuscularly using a sterile needle and syringe. Discard vial after use.

For single-dose prefilled syringes, securely attach a needle by twisting in a clockwise direction and administer dose of RECOMBIVAX HB intramuscularly. Discard syringe after use.

The deltoid muscle is the preferred site for intramuscular injection for adults, adolescents and children 1 year of age and older whose deltoid is large enough for intramuscular injection. The anterolateral aspect of the thigh is the preferred site for intramuscular injection for infants younger than 1 year of age. RECOMBIVAX HB should not be administered in the gluteal region, as injections given in the buttocks have resulted in lower seroconversion rates than expected.{2}

RECOMBIVAX HB may be administered subcutaneously to persons at risk for hemorrhage following intramuscular injections (e.g., hemophiliacs). However, hepatitis B vaccines are known to result in lower antibody response when administered subcutaneously.{3} Additionally, when other aluminum-adsorbed vaccines have been administered subcutaneously, an increased incidence of local reactions including subcutaneous nodules has been observed. Therefore, consider subcutaneous administration only in persons who are at risk of hemorrhage following intramuscular injections.

Do not administer intravenously or intradermally.

2.3 Known or Presumed Exposure to Hepatitis B Virus

Known or Presumed Exposure to HBsAg

Refer to recommendations of the Advisory Committee on Immunization Practices (ACIP) and to the package insert for hepatitis B immune globulin (HBIG) for management of persons with known or presumed exposure to the hepatitis B virus (e.g., neonates born of infected mothers or persons who experienced percutaneous or permucosal exposure to the virus). When recommended, administer RECOMBIVAX HB and HBIG intramuscularly at separate sites (e.g., opposite anterolateral thighs for exposed neonates) as soon as possible after exposure. Administer additional doses of RECOMBIVAX HB (to complete a vaccination series) in accordance with ACIP recommendations.

2.4 Booster Vaccinations

The duration of the protective effect of RECOMBIVAX HB in healthy vaccinees is unknown at present and the need for booster doses is not yet defined. The ACIP provides recommendations for use of a booster dose or revaccination series in previously vaccinated individuals with known or presumed exposure to Hepatitis B Virus.

Consider a booster dose or revaccination with RECOMBIVAX HB Dialysis Formulation (blue color code) in predialysis/dialysis patients if the anti-HBs level is less than 10 mIU/mL at 1 to 2 months after the third dose. Assess the need for a booster dose annually by antibody testing, and give a booster dose when the anti-HBs level declines to less than 10 mIU/mL.{3}

3 DOSAGE FORMS AND STRENGTHS

RECOMBIVAX HB is a sterile suspension available in the following presentations:

- 0.5 mL (5 mcg) Pediatric/Adolescent Formulation single-dose vials and prefilled syringes
- 1 mL (10 mcg) Adult Formulation single-dose vials and prefilled syringes

RECOMBIVAX HB DIALYSIS FORMULATION is a sterile suspension available in the following presentation:

- 1 mL (40 mcg) single-dose vial [see Description (11) and How Supplied/Storage and Handling (16)]

4 CONTRAINDICATIONS

Do not administer RECOMBIVAX HB to individuals with a history of severe allergic or hypersensitivity reactions (e.g., anaphylaxis) after a previous dose of any hepatitis B-containing vaccine or to any component of RECOMBIVAX HB, including yeast [see Description (11)].

5 WARNINGS AND PRECAUTIONS

5.1 Hypersensitivity to Latex

The vial stopper and the syringe plunger stopper and tip cap contain dry natural latex rubber, which may cause allergic reactions in latex-sensitive individuals.

5.2 Apnea in Premature Infants

Apnea following intramuscular vaccination has been observed in some infants born prematurely. Decisions about when to administer an intramuscular vaccine, including RECOMBIVAX HB, to infants born prematurely should be based on consideration of the individual infant's medical status and the potential benefits and possible risks of vaccination. For RECOMBIVAX HB, this assessment should include consideration of the mother's hepatitis B antigen status and the high probability of maternal transmission of hepatitis B virus to infants born to mothers who are HBsAg positive if vaccination is delayed.

5.3 Infants Weighing Less Than 2000 g

Hepatitis B vaccination should be delayed until 1 month of age or hospital discharge in infants weighing <2000 g if the mother is documented to be HBsAg negative at the time of the infant's birth. Infants weighing <2000 g born to HBsAg positive or HBsAg unknown mothers should receive vaccine and hepatitis B immune globulin (HBIG) in accordance with ACIP recommendations if HBsAg status cannot be determined{3} [see Dosage and Administration (2)].

5.4 Prevention and Management of Allergic Vaccine Reactions

Appropriate medical treatment and supervision must be available to manage possible anaphylactic reactions following administration [see Contraindications (4)].

5.5 Limitations of Vaccine Effectiveness

Hepatitis B virus has a long incubation period. RECOMBIVAX HB may not prevent hepatitis B infection in individuals who have an unrecognized hepatitis B infection at the time of vaccination. Additionally, vaccination with RECOMBIVAX HB may not protect all individuals.

6 ADVERSE REACTIONS

In healthy infants and children (up to 10 years of age), the most frequently reported systemic adverse reactions (>1% injections), in decreasing order of frequency, were irritability, fever, diarrhea, fatigue/weakness, diminished appetite, and rhinitis. In healthy adults, injection site reactions and systemic adverse reactions were reported following 17% and 15% of the injections, respectively.

6.1 Clinical Trials Experience

Because clinical trials are conducted under widely varying conditions, adverse reaction rates observed in the clinical trials of a vaccine cannot be directly compared to rates in the clinical trials of another vaccine and may not reflect the rates observed in practice.

In three clinical studies, 434 doses of RECOMBIVAX HB, 5 mcg, were administered to 147 healthy infants and children (up to 10 years of age) who were monitored for 5 days after each dose. Injection site reactions and systemic adverse reactions were reported following 0.2% and 10.4% of the injections, respectively. The most frequently reported systemic adverse reactions (>1% injections), in decreasing order of frequency, were irritability, fever (≥101°F oral equivalent), diarrhea, fatigue/weakness, diminished appetite, and rhinitis.

In a study that compared the three-dose regimen (5 mcg) with the two-dose regimen (10 mcg) of RECOMBIVAX HB in adolescents, the overall frequency of adverse reactions was generally similar.

In a group of studies, 3258 doses of RECOMBIVAX HB, 10 mcg, were administered to 1252 healthy adults who were monitored for 5 days after each dose. Injection site reactions and systemic adverse reactions were reported following 17% and 15% of the injections, respectively. The following adverse reactions were reported:

Incidence Equal To or Greater Than 1% of Injections

GENERAL DISORDERS AND ADMINISTRATION SITE CONDITIONS

Injection site reactions consisting principally of soreness, and including pain, tenderness, pruritus, erythema, ecchymosis, swelling, warmth, nodule formation.

The most frequent systemic complaints include fatigue/weakness; headache; fever (≥100°F); malaise.

GASTROINTESTINAL DISORDERS

Nausea; diarrhea

RESPIRATORY, THORACIC AND MEDIASTINAL DISORDERS

Pharyngitis; upper respiratory infection

Incidence Less Than 1% of Injections

GENERAL DISORDERS AND ADMINISTRATION SITE CONDITIONS

Sweating; achiness; sensation of warmth; lightheadedness; chills; flushing

GASTROINTESTINAL DISORDERS

Vomiting; abdominal pains/cramps; dyspepsia; diminished appetite

RESPIRATORY, THORACIC AND MEDIASTINAL DISORDERS

Rhinitis; influenza; cough

NERVOUS SYSTEM DISORDERS

Vertigo/dizziness; paresthesia

SKIN AND SUBCUTANEOUS TISSUE DISORDERS

Pruritus; rash (non-specified); angioedema; urticaria

MUSCULOSKELETAL AND CONNECTIVE TISSUE DISORDERS

Arthralgia including monoarticular; myalgia; back pain; neck pain; shoulder pain; neck stiffness

BLOOD AND LYMPHATIC DISORDERS

Lymphadenopathy

PSYCHIATRIC DISORDERS

Insomnia/disturbed sleep

EAR AND LABYRINTH DISORDERS

Earache

RENAL AND URINARY DISORDERS

Dysuria

CARDIAC DISORDERS

Hypotension

6.2 Post-Marketing Experience

The following additional adverse reactions have been reported with use of the marketed vaccine. Because these reactions are reported voluntarily from a population of uncertain size, it is not possible to reliably estimate their frequency or establish a causal relationship to a vaccine exposure.

Immune System Disorders

Hypersensitivity reactions including anaphylactic/anaphylactoid reactions, bronchospasm, and urticaria have been reported within the first few hours after vaccination. An apparent hypersensitivity syndrome (serum-sickness-like) of delayed onset has been reported days to weeks after vaccination, including: arthralgia/arthritis (usually transient), fever, and dermatologic reactions such as urticaria, erythema multiforme, ecchymoses and erythema nodosum [see Warnings and Precautions (5.1)]. Autoimmune diseases including systemic lupus erythematosus (SLE), lupus-like syndrome, vasculitis, and polyarteritis nodosa have also been reported.

Gastrointestinal Disorders

Elevation of liver enzymes; constipation

Nervous System Disorders

Guillain-Barré syndrome; multiple sclerosis; exacerbation of multiple sclerosis; myelitis including transverse myelitis; seizure; febrile seizure; peripheral neuropathy including Bell's Palsy; radiculopathy; herpes zoster; migraine; muscle weakness; hypesthesia; encephalitis

Skin and Subcutaneous Disorders

Stevens-Johnson syndrome; alopecia; petechiae; eczema

Musculoskeletal and Connective Tissue Disorders

Arthritis

Pain in extremity

Blood and Lymphatic System Disorders

Increased erythrocyte sedimentation rate; thrombocytopenia

Psychiatric Disorders

Irritability; agitation; somnolence

Eye Disorders

Optic neuritis; tinnitus; conjunctivitis; visual disturbances; uveitis

Cardiac Disorders

Syncope; tachycardia

The following adverse reaction has been reported with another Hepatitis B Vaccine (Recombinant) but not with RECOMBIVAX HB: keratitis.

7 DRUG INTERACTIONS

7.1 Concomitant Administration with Other Vaccines

Do not mix RECOMBIVAX HB with any other vaccine in the same syringe or vial. Use separate injection sites and syringes for each vaccine.

In clinical trials in children, RECOMBIVAX HB was concomitantly administered with one or more of the following US licensed vaccines: Diphtheria, Tetanus and whole cell Pertussis; oral Poliomyelitis vaccine; Measles, Mumps, and Rubella Virus Vaccine, Live; Haemophilus b Conjugate Vaccine (Meningococcal Protein Conjugate)] or a booster dose of Diphtheria, Tetanus, acellular Pertussis. Safety and immunogenicity were similar for concomitantly administered vaccines compared to separately administered vaccines.

In another clinical trial, a related HBsAg-containing product, Haemophilus b Conjugate (Meningococcal Protein Conjugate) and Hepatitis B (Recombinant) combination product (no longer licensed), was given concomitantly with eIPV (enhanced inactivated Poliovirus vaccine) or VARIVAX® [Varicella Virus Vaccine Live (Oka/Merck)], using separate sites and syringes for injectable vaccines. No serious vaccine-related adverse events were reported, and no impairment of immune response to these individually tested vaccine antigens was demonstrated.

The Haemophilus b Conjugate (Meningococcal Protein Conjugate) and Hepatitis B (Recombinant) combination product (no longer licensed) has also been administered concomitantly with the primary series of DTaP to a limited number of infants. No serious vaccine-related adverse events were reported.

7.2 Concomitant Administration with Immune Globulin

RECOMBIVAX HB may be administered concomitantly with HBIG. The first dose of RECOMBIVAX HB may be given at the same time as HBIG, but the injections should be administered at different sites.

7.3 Interference with Laboratory Tests

Hepatitis B surface antigen (HBsAg) derived from hepatitis B vaccines has been transiently detected in blood samples following vaccination. Serum HBsAg detection may not have diagnostic value within 28 days after receipt of a hepatitis B vaccine, including RECOMBIVAX HB.

8 USE IN SPECIFIC POPULATIONS

8.1 Pregnancy

Risk Summary

All pregnancies have a risk of birth defect, loss, or other adverse outcomes. In the US general population, the estimated background risk of major birth defects and miscarriage in clinically recognized pregnancies is 2% to 4%, and 15% to 20%, respectively.

There are no adequate and well-controlled studies designed to evaluate RECOMBIVAX HB in pregnant women. Available post-approval data do not suggest an increased risk of miscarriage or major birth defects in women who received RECOMBIVAX HB during pregnancy.

Developmental toxicity studies have not been conducted with the vaccine in animals.

Data

Human Data

In post-licensure clinical studies of RECOMBIVAX HB, 26 pregnant women were inadvertently administered RECOMBIVAX HB following their last menstrual period. Among these pregnancies, after excluding elective terminations (n=3), there were 23 pregnancies with known outcomes all with exposure in the first trimester. Miscarriage was reported in 4 of 23 (17%) pregnancies and major birth defects were reported in 0 of 19 (0%) live births. The rates of miscarriage and major birth defects were consistent with estimated background rates.

Post-approval adverse reactions are reported voluntarily from a population of uncertain size. It is not always possible to reliably estimate their frequency or establish a causal relationship to the vaccine.

In prospectively reported spontaneous post-approval reports from 1986 to 2018, 105 women with known pregnancy outcomes were exposed to RECOMBIVAX HB during pregnancy following the last menstrual period. After excluding induced abortions (n=5), those with exposure in the third trimester (n=4), and those with an unknown exposure timing (n=6), there were 90 pregnancies with known outcomes with exposures in the first or second trimester. Miscarriage was reported for 7 of 90 (7.8%) pregnancies. Major birth defects were reported for 2 of 83 (2.4%) live born infants. The rates of miscarriage and major birth defects were consistent with estimated background rates.

8.2 Lactation

Risk Summary

It is not known whether RECOMBIVAX HB is excreted in human milk. Data are not available to assess the effects of RECOMBIVAX HB on the breastfed infant or on milk production/excretion.

The developmental and health benefits of breastfeeding should be considered along with the mother's clinical need for RECOMBIVAX HB and any potential adverse effects on the breastfed child from RECOMBIVAX HB or from the underlying maternal condition. For preventive vaccines, the underlying maternal condition is susceptibility to the disease prevented by the vaccine.

8.4 Pediatric Use

Safety and effectiveness of RECOMBIVAX HB have been established in all pediatric age groups. Maternally transferred antibodies do not interfere with the active immune response to the vaccine. [See Adverse Reactions (6.1) and Clinical Studies (14.1 and 14.2).] The safety and effectiveness of RECOMBIVAX HB Dialysis Formulation in children have not been established.

8.5 Geriatric Use

Clinical studies of RECOMBIVAX HB used for licensure did not include sufficient numbers of subjects 65 years of age and older to determine whether they respond differently from younger subjects. However, in later studies it has been shown that a diminished antibody response can be expected in persons older than 60 years of age.

11 DESCRIPTION

RECOMBIVAX HB Hepatitis B Vaccine (Recombinant) is a sterile suspension of non-infectious subunit viral vaccine derived from HBsAg produced in yeast cells. A portion of the hepatitis B virus gene, coding for HBsAg, is cloned into yeast, and the vaccine for hepatitis B is produced from cultures of this recombinant yeast strain according to methods developed in the Research Laboratories of Merck Sharp & Dohme LLC, Rahway, NJ, USA.

The antigen is harvested and purified from fermentation cultures of a recombinant strain of the yeast Saccharomyces cerevisiae containing the gene for the adw subtype of HBsAg. The fermentation process involves growth of Saccharomyces cerevisiae on a complex fermentation medium which consists of an extract of yeast, soy peptone, dextrose, amino acids and mineral salts. The HBsAg protein is released from the yeast cells by cell disruption and purified by a series of physical and chemical methods. The purified protein is treated in phosphate buffer with formaldehyde and then coprecipitated with alum (potassium aluminum sulfate) to form bulk vaccine adjuvanted with amorphous aluminum hydroxyphosphate sulfate. Each dose contains less than 1% yeast protein. The vaccine produced by the Merck Sharp & Dohme LLC, Rahway, NJ, USA method has been shown to be comparable to the plasma-derived vaccine in terms of animal potency (mouse, monkey, and chimpanzee) and protective efficacy (chimpanzee and human).

The vaccine against hepatitis B, prepared from recombinant yeast cultures, is free of association with human blood or blood products.

RECOMBIVAX HB Hepatitis B Vaccine (Recombinant) is supplied in three formulations. [See How Supplied/Storage and Handling (16).]

Pediatric/Adolescent Formulation (Without Preservative), 10 mcg/mL: each 0.5 mL dose contains 5 mcg of hepatitis B surface antigen.

Adult Formulation (Without Preservative), 10 mcg/mL: each 1 mL dose contains 10 mcg of hepatitis B surface antigen.

Dialysis Formulation (Without Preservative), 40 mcg/mL: each 1 mL dose contains 40 mcg of hepatitis B surface antigen.

All formulations contain approximately 0.5 mg of aluminum (provided as amorphous aluminum hydroxyphosphate sulfate, previously referred to as aluminum hydroxide) per mL of vaccine. In each formulation, hepatitis B surface antigen is adsorbed onto approximately 0.5 mg of aluminum (provided as amorphous aluminum hydroxyphosphate sulfate) per mL of vaccine. The vaccine contains <15 mcg/mL residual formaldehyde. The vaccine is of the adw subtype.

12 CLINICAL PHARMACOLOGY

12.1 Mechanism of Action

RECOMBIVAX HB has been shown to elicit antibodies to hepatitis B virus as measured by ELISA.

Antibody concentrations ≥10mIU/mL against HBsAg are recognized as conferring protection against hepatitis B infection.{2}

Infection with hepatitis B virus can have serious consequences including acute massive hepatic necrosis and chronic active hepatitis. Chronically infected persons are at increased risk for cirrhosis and hepatocellular carcinoma.

13 NONCLINICAL TOXICOLOGY

13.1 Carcinogenesis, Mutagenesis, Impairment of Fertility

RECOMBIVAX HB has not been evaluated for its carcinogenic or mutagenic potential, or its potential to impair fertility [see Use in Specific Populations (8)].

14 CLINICAL STUDIES

14.1 Efficacy in Neonates with Peripartum Exposure to Hepatitis B

The protective efficacy of three 5 mcg doses of RECOMBIVAX HB has been demonstrated in neonates born of mothers positive for both HBsAg and HBeAg (a core-associated antigenic complex which correlates with high infectivity). In a clinical study of infants who received one dose of HBIG at birth followed by the recommended three-dose regimen of RECOMBIVAX HB, chronic infection had not occurred in 96% of 130 infants after nine months of follow-up.{4} The estimated efficacy in prevention of chronic hepatitis B infection was 95% as compared to the infection rate in untreated historical controls.{5} Significantly fewer neonates became chronically infected when given one dose of HBIG at birth followed by the recommended three-dose regimen of RECOMBIVAX HB when compared to historical controls who received only a single dose of HBIG.{6} As demonstrated in the above study, HBIG, when administered simultaneously with RECOMBIVAX HB at separate body sites, did not interfere with the induction of protective antibodies against hepatitis B virus elicited by the vaccine.{6}

14.2 Immunogenicity of a Three-Dose Regimen in Healthy Infants, Children, and Adolescents

Three 5 mcg doses of RECOMBIVAX HB induced a protective level of antibody in 100% of 92 infants, 99% of 129 children, and in 99% of 112 adolescents [see Dosage and Administration (2.3)].

14.3 Immunogenicity of a Two-Dose Regimen in Healthy Adolescents 11 through 15 Years of Age

For adolescents (11 through 15 years of age), the immunogenicity of a two-dose regimen (10 mcg at 0 and 4-6 months) was compared with that of the standard three-dose regimen (5 mcg at 0, 1, and 6 months) in an open, randomized, multicenter study. The proportion of adolescents receiving the two-dose regimen who developed a protective level of antibody one month after the last dose (99% of 255 subjects) appears similar to that among adolescents who received the three-dose regimen (98% of 121 subjects). After adolescents (11 through 15 years of age) received the first 10-mcg dose of the two-dose regimen, the proportion who developed a protective level of antibody was approximately 72%.

14.4 Immunogenicity in Healthy Adults

Clinical studies have shown that RECOMBIVAX HB when injected into the deltoid muscle induced protective levels of antibody in 96% of 1213 healthy adults who received the recommended three-dose regimen. Antibody responses varied with age; a protective level of antibody was induced in 98% of 787 young adults 20-29 years of age, 94% of 249 adults 30-39 years of age and in 89% of 177 adults ≥40 years of age.

14.5 Efficacy and Immunogenicity in Specific Populations

Chronic Hepatitis C Infection

In one published study, the seroprotection rates in individuals with chronic hepatitis C virus (HCV) infection given the standard regimen of RECOMBIVAX HB was approximately 70%.{7} In a second published study of intravenous drug users given an accelerated schedule of RECOMBIVAX HB, infection with HCV did not affect the response to RECOMBIVAX HB.{8}

Predialysis and Dialysis Adult Patients

Predialysis and dialysis adult patients respond less well to hepatitis B vaccines than do healthy individuals; however, vaccination of adult patients early in the course of their renal disease produces higher seroconversion rates than vaccination after dialysis has been initiated.{9} In addition, the responses to these vaccines may be lower if the vaccine is administered as a buttock injection. When 40 mcg of Hepatitis B Vaccine (Recombinant), was administered in the deltoid muscle, 89% of 28 participants developed anti-HBs with 86% achieving levels ≥10 mIU/mL. However, when the same dosage of this vaccine was administered inappropriately either in the buttock or a combination of buttock and deltoid, 62% of 47 participants developed anti-HBs with 55% achieving levels of ≥10 mIU/mL.

15 REFERENCES

1. CDC. A Comprehensive Strategy to Eliminate Transmission of Hepatitis B Virus Infection in the United States. Recommendations of the Advisory Committee on Immunization Practices (ACIP) Part I: Immunization of Infants, Children and Adolescents. MMWR Recommendations and Reports 2005; 54(RR16): 1-23. Appendix C - Postexposure Prophylaxis of Persons with Discrete Identifiable Exposures to Hepatitis B Virus (HBV) and http://www.cdc.gov/hepatitis/hbv/pdfs/correctedtable4.pdf
2. CDC. Suboptimal Response to Hepatitis B Vaccine given by Injection into the Buttock. MMWR Weekly Report 1985; 34: 105-8, 113.
3. Centers for Disease Control and Prevention. A Comprehensive Immunization Strategy to Eliminate Transmission of Hepatitis B Virus Infection in the United States. Recommendations of the Advisory Committee on Immunization Practices (ACIP). Part 2: Immunization of Adults, MMWR 2006, 55(RR-16): 1-25.
4. Stevens, C.E.; Taylor, P.E.; Tong, M.J., et al.: Prevention of Perinatal Hepatitis B Virus Infection with Hepatitis B Immune Globulin and Hepatitis B Vaccine, in Zuckerman, A.J. (ed.), "Viral Hepatitis and Liver Diseases", Alan R. Liss, 982-983, 1988.
5. Stevens, C.E.; Taylor, P.E.; Tong, M.J., et al.: Yeast-Recombinant Hepatitis B Vaccine, Efficacy with Hepatitis B Immune Globulin in Prevention of Perinatal Hepatitis B Virus Transmission, JAMA 257(19): 2612-2616, 1987.
6. Beasley, R.P.; Hwang, L.; Stevens, C.E.; Lin, C.; Hsieh, F.; Wang, K.; Sun, T.; Szmuness, W.: Efficacy of Hepatitis B Immune Globulin for Prevention of Perinatal Transmission of the Hepatitis B Virus Carrier State: Final Report of a Randomized Double-Blind, Placebo-Controlled Trial, Hepatology 3: 135-141, 1983.
7. Wiedmann, M.; Liebert, U.G.; Oesen, U.; Porst, H.; Wiese, M.; Schroeder, S.; Halm, U.; Mossner, J.; Berr, F.: Decreased Immunogenicity of Recombinant Hepatitis B Vaccine in Chronic Hepatitis C, Hepatology, 31: 230-234, 2000.
8. Minniti, F.; Baldo, V.; Trivello, R.; Bricolo, R.; Di Furia, L.; Renzulli, G.; Chiaramonte, M.: Response to HBV vaccine in Relation to anti-HCV and anti-HBc Positivity: a Study in Intravenous Drug Addicts, Vaccine, 17: 3083-3085, 1999.
9. Recommendations of the Advisory Committee on Immunization Practices (ACIP): Hepatitis B Virus Infection: A Comprehensive Strategy to Eliminate Transmission in the United States, 1996 update, MMWR (draft January 13, 1996).

16 HOW SUPPLIED/STORAGE AND HANDLING

16.1 How Supplied

RECOMBIVAX HB (pediatric and adult) FORMULATION is available in single-dose vials and prefilled Luer-Lok® syringes.

RECOMBIVAX HB DIALYSIS FORMULATION is available in single-dose vials.

Pediatric/Adolescent Formulation (PRESERVATIVE FREE)

0.5 mL (5 mcg) in single-dose vials and prefilled Luer-Lok® syringes

NDC 0006-4981-00 – box of ten 0.5-mL single-dose vials

Color coded with a yellow cap and stripe on the vial labels and cartons and an orange banner on the vial labels and cartons

NDC 0006-4093-02 – carton of 10 prefilled single-dose Luer-Lok® syringes with tip caps

Color coded with a yellow plunger rod

Adult Formulation (PRESERVATIVE FREE)

1 mL (10mcg) in single-dose vials and prefilled Luer-Lok® syringes

NDC 0006-4995-00 – 1-mL single dose vial

Color coded with a green cap and stripe

NDC 0006-4995-41 – box of ten 1-mL single-dose vials

Color coded with a green cap and stripe

NDC 0006-4094-02 – carton of 10 pre-filled single-dose syringes with tip caps

Color coded with a green plunger rod

RECOMBIVAX HB DIALYSIS FORMULATION

1 mL (40mcg) in single-dose vials

NDC 0006-4992-00 – 1-mL single-dose vial

Color coded with a blue cap and stripe

16.2 Storage and Handling

- Protect from light.
- Store vials and syringes at 2-8°C (36-46°F).
- Do not freeze since freezing destroys potency.
- RECOMBIVAX HB is stable at temperatures from 0° to 25° C (32° to 77°F) for 72 hours. These data are not recommendations for shipping or storage but may guide decisions for use in case of temporary temperature excursions.

17 PATIENT COUNSELING INFORMATION

Information for Vaccine Recipients and Parents/Guardians

- Inform the patient, parent or guardian of the potential benefits and risks associated with vaccination, as well as the importance of completing the immunization series.
- Question the vaccine recipient, parent or guardian about the occurrence of any symptoms and/or signs of adverse reaction after a previous dose of hepatitis B vaccine.
- Tell the patient, parent or guardian to report adverse events to the physician or clinic where the vaccine was administered.
- Prior to vaccination, give the patient, parent or guardian the Vaccine Information Statements which are required by the National Vaccine Injury Act of 1986. The materials are available free of charge at the Centers for Disease Control and Prevention (CDC) website (www.cdc.gov/vaccines).
- Tell the patient, parent or guardian that the United States Department of Health and Human Services has established a Vaccine Adverse Event Reporting System (VAERS) to accept all reports of suspected adverse events after the administration of any vaccine, including but not limited to the reporting of events by the National Childhood Vaccine Injury Act of 1986. The VAERS toll-free number is 1-800-822-7967. Reporting forms may also be obtained at the VAERS website at www.vaers.hhs.gov .

Manufactured and Distributed by: Merck Sharp & Dohme LLC
Rahway, NJ 07065, USA

For patent information: www.msd.com/research/patent

The trademarks depicted herein are owned by their respective companies.

Copyright © 1986-2023 Merck & Co., Inc., Rahway, NJ, USA, and its affiliates.
All rights reserved.

uspi-v232-i-2304r443

PRINCIPAL DISPLAY PANEL - 0.5 mL Vial Carton

NDC 0006-4981-00
10 Single-dose 5 mcg/0.5 mL Vials

HEPATITIS B VACCINE
[RECOMBINANT]
RECOMBIVAX HB®

PEDIATRIC/ADOLESCENT

No Preservative

This package contains 10 single-dose vials. Each 0.5 mL vial contains 5 mcg of hepatitis B surface antigen on an aluminum
hydroxide adjuvant. Vaccine is prepared from fermentation cultures of a recombinant strain of the yeast Saccharomyces
cerevisiae containing the gene for the adw subtype of HBsAg. This Product Contains No Preservatives.

Rx only

PRINCIPAL DISPLAY PANEL - 0.5 mL Syringe Carton

NDC 0006-4093-02
10 Single-Dose 0.5-mL Syringes

HEPATITIS B VACCINE
[RECOMBINANT]
RECOMBIVAX HB®

PEDIATRIC/ADOLESCENT FORMULATION

No Preservative

This package contains 10 single-dose syringes. Each 0.5-mL syringe contains
5 mcg of hepatitis B surface antigen adjuvanted with amorphous aluminum
hydroxyphosphate sulfate.

Vaccine is prepared from fermentation cultures of a recombinant strain of the yeast
Saccharomyces cerevisiae containing the gene for the adw subtype of HBsAg.

This Product Contains No Thimerosal.
Rx only

PRINCIPAL DISPLAY PANEL - 1 mL Vial Carton

NDC 0006-4995-00
1 Single-dose
10 mcg/1 mL Vial

HEPATITIS B
VACCINE
[RECOMBINANT]
RECOMBIVAX HB®

ADULT
FORMULATION

Preservative Free

1 mL contains 10 mcg of hepatitis B
surface antigen adjuvanted with
amorphous aluminum
hydroxyphosphate sulfate.

Vaccine is prepared from fermentation
cultures of a recombinant strain of
the yeast Saccharomyces cerevisiae
containing the gene for the adw
subtype of HBsAg.

This Product Contains No Thimerosal.

Rx only

PRINCIPAL DISPLAY PANEL - 1.0 mL Syringe Carton

NDC 0006-4094-02
10 Single-Dose 1.0-mL Syringes

HEPATITIS B VACCINE
[RECOMBINANT]
RECOMBIVAX HB®

ADULT FORMULATION

No Preservative

This package contains 10 single-dose syringes. Each 1.0-mL syringe contains
10 mcg of hepatitis B surface antigen adjuvanted with amorphous aluminum
hydroxyphosphate sulfate.

Vaccine is prepared from fermentation cultures of a recombinant strain of the yeast
Saccharomyces cerevisiae containing the gene for the adw subtype of HBsAg.

This Product Contains No Thimerosal.
Rx only

PRINCIPAL DISPLAY PANEL - 1 mL Vial Carton

NDC 0006-4992-00
1 Single-dose
40 mcg/1 mL Vial

HEPATITIS B
VACCINE
[RECOMBINANT]
RECOMBIVAX HB®

DIALYSIS
FORMULATION

No Preservative

1 mL contains 40 mcg of hepatitis B
surface antigen adjuvanted with
amorphous aluminum
hydroxyphosphate sulfate.

Vaccine is prepared from fermentation
cultures of a recombinant strain of
the yeast Saccharomyces cerevisiae
containing the gene for the adw
subtype of HBsAg.

This Product Contains No Thimerosal.

Rx only

PRINCIPAL DISPLAY PANEL - 1 mL Vial Carton

NDC 0006-4995-41
10 Single-dose 10 mcg/1 mL Vials

HEPATITIS B VACCINE (RECOMBINANT)
RECOMBIVAX HB®

No Preservative

ADULT FORMULATION

This package contains 10 single-dose vials. Each 1 mL vial contains 10 mcg of hepatitis B surface antigen
adjuvanted with amorphous aluminum hydroxyphosphate sulfate. Vaccine is prepared from fermentation
cultures of a recombinant strain of the yeast Saccharomyces cerevisiae containing the gene for the
adw subtype of HBsAg. This Product Contains No Thimerosal.

Rx only